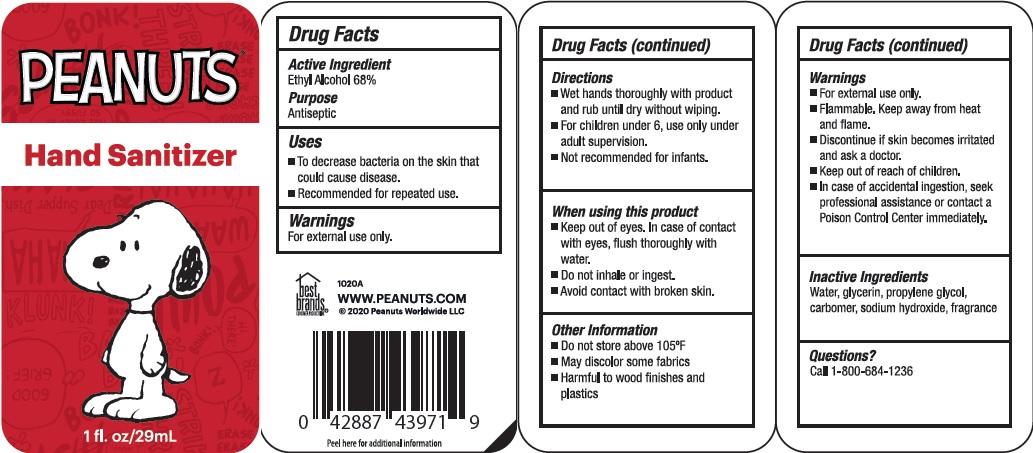 DRUG LABEL: Peannuts Hand Sanitizer
NDC: 74274-120 | Form: LIQUID
Manufacturer: Huizhou Bliss Commodity Co., Ltd
Category: otc | Type: HUMAN OTC DRUG LABEL
Date: 20201203

ACTIVE INGREDIENTS: ALCOHOL 68 mL/100 mL
INACTIVE INGREDIENTS: WATER; GLYCERIN; PROPYLENE GLYCOL; SODIUM HYDROXIDE

Active ingredient

Ethyl Alcohol 68%

Purpose

Antiseptic

Uses

- To decrease bacteria on the skin that could cause disease.
- Recommended for repeated use.

KEEP OUT OF REACH OF CHILDREN

if swallowed, get medical help or contact a Poison Control Center right away.

warnings:

- Flamable, keep away from heat and flame
- For external use only.
- Discontinue if skin away from heat and flame.
- Keep out of reach of children
- In case of accidental ingestion, seek professional assistance or contact a Poison Control Center immediately

When using this product

- keep out of eyes. In case of contact with eyes, flush thoroughly with water
- Avoid contact with broken skin
- Do not inhale or ingest

Other Information:

- Do not store above 105℃
- May discolor some fabrics
- Harmful to wood finishes and plastics

Directions

- Wet hands thoroughly with product and rub unitl dry without wiping.
- For children under 6, use only under adult supervision.
- Not recommended for infants.

Inactive ingredients

Water, Glycerin, Carbomer, Propylene Glycol, Sodium Hydroxide, Fragrance